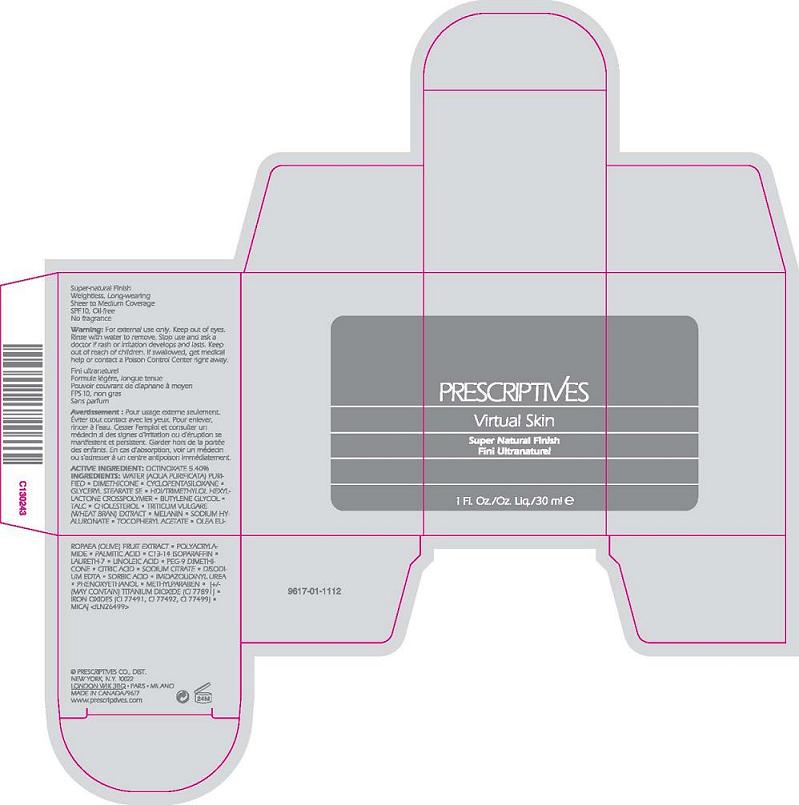 DRUG LABEL: VIRTUAL SKIN 
NDC: 59158-759 | Form: LIQUID
Manufacturer: PRESCRIPTIVES INC.
Category: otc | Type: HUMAN OTC DRUG LABEL
Date: 20120424

ACTIVE INGREDIENTS: OCTINOXATE 5.4 mL/100 mL
INACTIVE INGREDIENTS: WATER; DIMETHICONE; CYCLOMETHICONE 5; GLYCERYL MONOSTEARATE; BUTYLENE GLYCOL; TALC; CHOLESTEROL; WHEAT BRAN; HYALURONATE SODIUM; ALPHA-TOCOPHEROL ACETATE; BLACK OLIVE; POLYACRYLAMIDE (10000 MW); PALMITIC ACID; C13-14 ISOPARAFFIN; CAPRYLYL GLYCOL; LAURETH-7; HEXYLENE GLYCOL; LINOLEIC ACID; SILICON DIOXIDE; CITRIC ACID MONOHYDRATE; EDETATE DISODIUM; SORBIC ACID; POTASSIUM SORBATE; PHENOXYETHANOL; TITANIUM DIOXIDE; FERRIC OXIDE RED; MICA

ACTIVE INGREDIENT: OCTINOXATE 5.40%

INACTIVE INGREDIENT

INACTIVE INGREDIENTS: WATER\AQUA\EAU [] DIMETHICONE [] CYCLOPENTASILOXANE [] GLYCERYL STEARATE SE [] HDI/TRIMETHYLOL HEXYLLACTONE CROSSPOLYMER [] BUTYLENE GLYCOL [] TALC [] CHOLESTEROL [] TRITICUM VULGARE (WHEAT BRAN) EXTRACT [] MELANIN [] SODIUM HYALURONATE [] TOCOPHERYL ACETATE [] OLEA EUROPAEA (OLIVE) FRUIT EXTRACT [] POLYACRYLAMIDE [] ETHYLHEXYLGLYCERIN [] PALMITIC ACID [] C13-14 ISOPARAFFIN [] CAPRYLYL GLYCOL [] LAURETH-7 [] HEXYLENE GLYCOL [] LINOLEIC ACID [] PEG-9 DIMETHICONE [] SILICA [] CITRIC ACID [] SODIUM CITRATE [] DISODIUM EDTA [] SORBIC ACID [] BENZOIC ACID [] POTASSIUM SORBATE [] PHENOXYETHANOL [] [+/- TITANIUM DIOXIDE (CI 77891) [] IRON OXIDES (CI 77491, CI 77492, CI 77499) [] MICA

WARNINGS

WARNINGS: FOR EXTERNAL USE ONLY. KEEP OUT OF EYES. RINSE WITH WATER TO REMOVE. STOP USE AND ASK A DOCTOR IF SKIN RASH OR IRRITATION OCCURS. KEEP OUT OF REACH OF CHILDREN. IF SWALLOWED, GET MEDICAL HELP OR CONTACT A POISON CONTROL CENTER RIGHT AWAY.

PACKAGE LABEL

PRESCRIPTIVES
VIRTUAL SKIN
SUPER NATURAL FINISH
SPF 10
1.0 FL OZ LIQ/ 30 ML
PRESCRIPTIVES CO. DIST
NY NY 10022